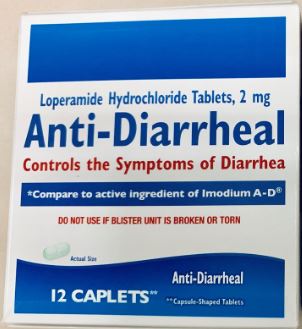 DRUG LABEL: First Aid Direct Anti-Diarrheal
NDC: 42961-103 | Form: CAPSULE
Manufacturer: Cintas Corp
Category: otc | Type: HUMAN OTC DRUG LABEL
Date: 20250929

ACTIVE INGREDIENTS: LOPERAMIDE HYDROCHLORIDE 2 mg/1 1
INACTIVE INGREDIENTS: STARCH, CORN; D&C YELLOW NO. 10 ALUMINUM LAKE; DIBASIC CALCIUM PHOSPHATE DIHYDRATE; FD&C BLUE NO. 1; MAGNESIUM STEARATE; MICROCRYSTALLINE CELLULOSE; SILICON DIOXIDE

Active Ingredient (in each caplet)

Loperamide HCl 2mg

Purpose

Anti-diarrheal

Use

controls symptoms of diarrhea, including Travelers' Diarrhea

Warnings

Allergy alert: Do not use if you have ever had a rash or other allergic reaction to Loperamide HCl

Heart alert: Taking more than directed can cause serious heart problems or death

Do not use if you have bloody or black stool

Ask a doctor before use if you have

- fever
- mucus in the stool
- a history of liver disease

Ask a doctor or pharmacist before use if you are taking antibiotics

When using this product tiredness, drowsiness or dizziness may occur. Be careful when driving or operating machinery.

Stop use and ask a doctor if

- symptoms get worse
- diarrhea lasts for more than 2 days
- you get abdominal swelling or bulging

These may be signs of a serious condition.

PREGNANCY OR BREAST FEEDING

If pregnant or breast-feeding, ask a health professional before use.

Keep out of reach of children. In case of overdose, get medical help or contact a Poison Control Center right away (1-800-222-1222).

Directions

- drink plenty of clear fluids to help prevent dehydration caused by diarrhea
- find right dose on chart. If possible, use weight to dose; otherwise, use age.

adults and children 12 years and over | 2 caplets after the first loose stool; 1 caplet after each subsequent loose stool; but no more than 4 caplets in 24 hours
children 9-11 years (60-95 lbs) | 1 caplet after the first loose stool; 1/2 caplet after each subsequent loose stool; but no more than 3 caplets in 24 hours
children 6-8 years (48-59 lbs) | 1 caplet after the first loose stool; 1/2 caplet after each subsequent loose stool; but no more than 2 caplets in 24 hours
children 2-5 years (34-47 lbs) | ask a doctor
children under 2 years (up to 33 lbs) | do not use

Other information

- store at 20°-25°C (68°-77°F)
- avoid excessive heat above 40°C (104°F)
- do not use blister unit is broken or torn

Inactive Ingredients

corn starch, D&C yellow #10 aluminum lake, dicalcium phosphate dihydrate, FD&C blue #1 brilliant blue lake, magnesium stearate, microcrystalline cellulose, silica gel

PACKAGE LABEL

Loperamide Hydrochloride Tablets, 2 mg

Anti-Diarrheal

Controls the Symptoms of Diarrhea

*Compare to active ingredient of Imodium A-D®
DO NOT USE IF BLISTER UNIT IS BROKEN OR TORN

Actual size

12 CAPLETS** Anti-Diarrheal

**Capsule-Shaped Tablet